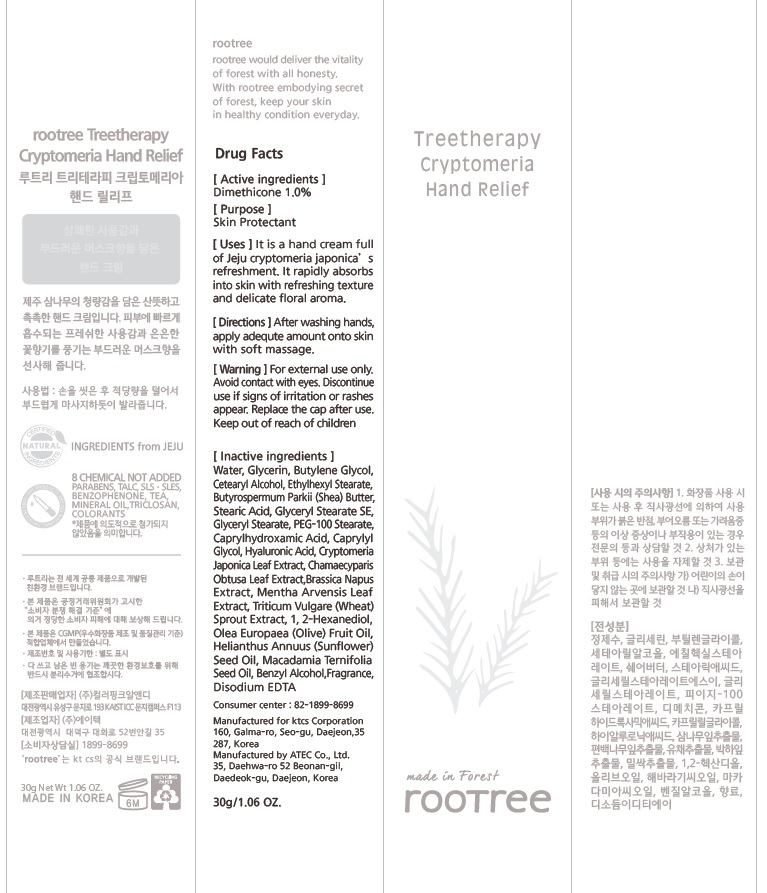 DRUG LABEL: rootree Treetherapy Cryptomeria Hand Relief
NDC: 72441-030 | Form: CREAM
Manufacturer: KTCS Corporation
Category: otc | Type: HUMAN OTC DRUG LABEL
Date: 20180730

ACTIVE INGREDIENTS: Dimethicone 0.3 g/30 g
INACTIVE INGREDIENTS: Water; Glycerin

ACTIVE INGREDIENT

Active ingredients: Dimethicone 1.0%

INACTIVE INGREDIENT

Inactive ingredients:

Water,Glycerin,Butylene Glycol,Cetearyl Alcohol,Ethylhexyl Stearate,Butyrospermum Parkii (Shea) Butter,Stearic Acid,Glyceryl Stearate SE,Glyceryl Stearate,PEG-100 Stearate,Caprylhydroxamic Acid,Caprylyl Glycol,Hyaluronic Acid,Cryptomeria Japonica Leaf Extract,Chamaecyparis Obtusa Leaf Extract,Brassica Napus Extract,Mentha Arvensis Leaf Extract,Triticum Vulgare (Wheat) Sprout Extract,1,2-Hexanediol,Olea Europaea (Olive) Fruit Oil,Helianthus Annuus (Sunflower) Seed Oil,Macadamia Ternifolia Seed Oil,Benzyl Alcohol,Fragrance,Disodium EDTA

PURPOSE

Purpose: Skin Protectant

WARNINGS

For external use only.

Avoid contact with eyes.

Discontinue use if signs of irritation or rashes appear.

Replace the cap after use.

Keep out of reach of children

KEEP OUT OF REACH OF CHILDREN

Uses

It is a hand cream full of Jeju cryptomeria japonica’s refreshment. It rapidly absorbs into skin with refreshing texture and delicate floral aroma.

Directions

After washing hands, apply adequte amount onto skin with soft massage.